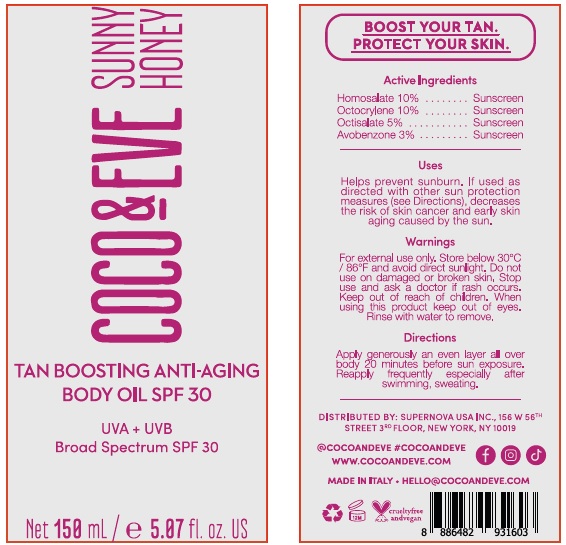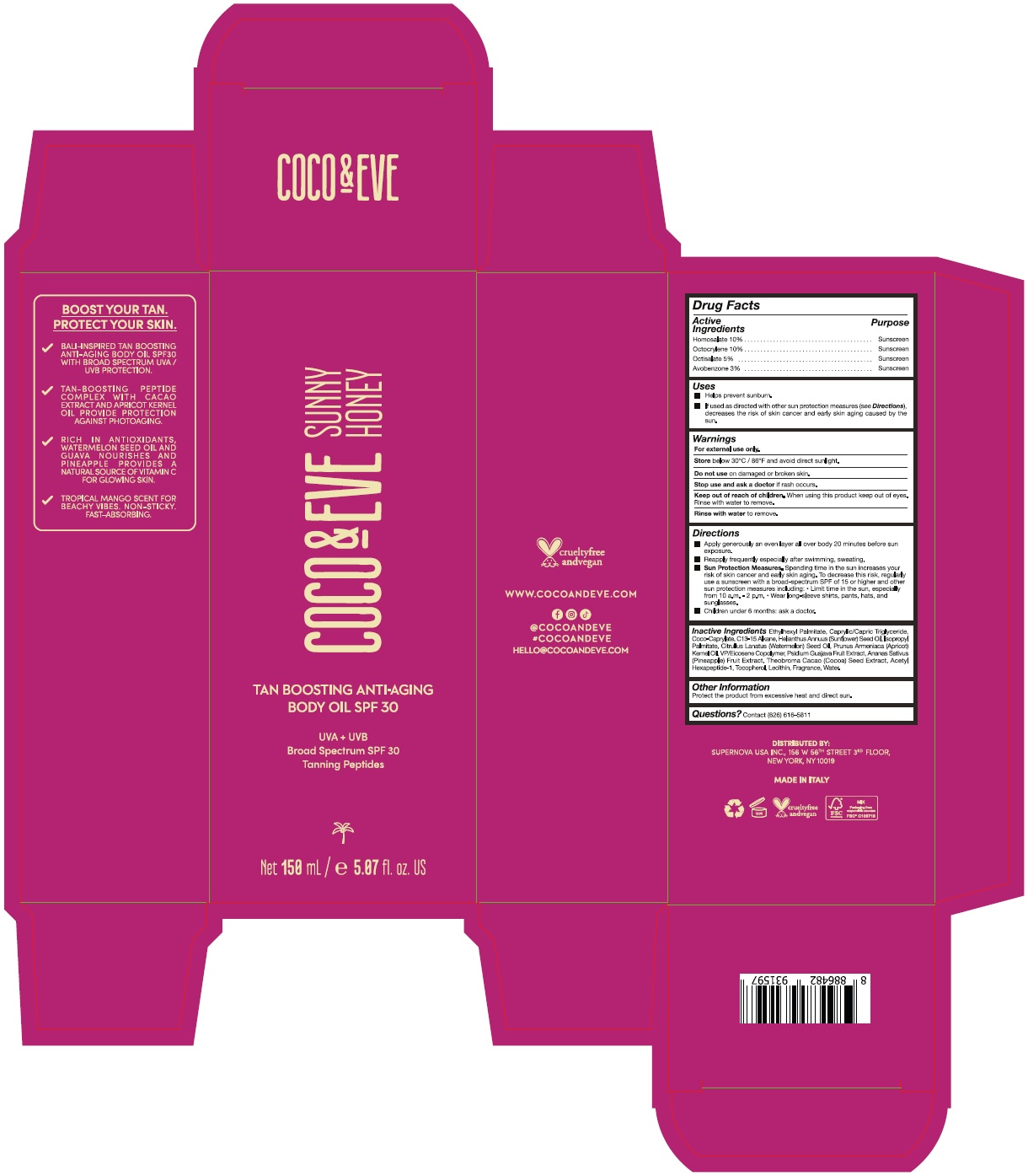 DRUG LABEL: coco and eve tan boosting anti-aging body oil spf 30
NDC: 82931-005 | Form: LOTION
Manufacturer: Supernova USA Inc.
Category: otc | Type: HUMAN OTC DRUG LABEL
Date: 20230605

ACTIVE INGREDIENTS: HOMOSALATE 10 g/100 mL; OCTOCRYLENE 10 g/100 mL; OCTISALATE 5 g/100 mL; AVOBENZONE 3 g/100 mL
INACTIVE INGREDIENTS: ETHYLHEXYL PALMITATE; C13-15 ALKANE; MEDIUM-CHAIN TRIGLYCERIDES; COCO-CAPRYLATE; SUNFLOWER OIL; ISOPROPYL PALMITATE; WATERMELON SEED OIL; APRICOT KERNEL OIL; VINYLPYRROLIDONE/EICOSENE COPOLYMER; TOCOPHEROL; LECITHIN, SOYBEAN; PINEAPPLE; GUAVA; COCOA; FRAGRANCE 13576; WATER; ACETYL HEXAPEPTIDE-1

COCO & EVE TAN BOOSTING ANTI-AGING BODY OIL SPF 30

Drug Facts

Active Ingredients
Homosalate 10%
Octocrylene 10%
Octisalate 5%
Avobenzone 3%

Purpose
Sunscreen
Sunscreen
Sunscreen
Sunscreen

Uses

- Helps prevent sunburn.
- If used as directed with other sun protection measures (see Directions), decreases the risk of skin cancer and early skin aging caused by the sun.

Warnings

For external use only.

Store below 30°C / 86°F and avoid direct sunlight.

Do not use on damaged or broken skin.

Stop use and ask a doctor if rash occurs.

Keep out of reach of children. When using this product keep out of eyes. Rinse with water to remove.

Rinse with water to remove.

Directions

- Apply generously an even layer all over body 20 minutes before sun exposure.
- Reapply frequently especially after swimming, sweating.
- Sun Protection Measures. Spending time in the sun increases your risk of skin cancer and early skin aging. To decrease this risk, regularly use a sunscreen with a broad-spectrum SPF of 15 or higher and other sun protection measures including:
  - Limit time in the sun, especially from 10 a.m. - 2 p.m.
  - Wear long-sleeve shirts, pants, hats, and sunglasses.
- Children under 6 months: ask a doctor.

INACTIVE INGREDIENT

Inactive Ingredients Ethylhexyl Palmitate, Caprylic/Capric Triglyceride, Coco-Caprylate, C13-15 Alkane, Helianthus Annuus (Sunflower) Seed Oil, Isopropyl Palmitate, Citrullus Lanatus (Watermelon) Seed Oil, Prunus Armeniaca (Apricot) Kernel Oil, VP/Eicosene Copolymer, Psidium Guajava Fruit Extract, Ananas Sativus (Pineapple) Fruit Extract, Theobroma Cacao (Cocoa) Seed Extract, Acetyl Hexapeptide-1, Tocopherol, Lecithin, Fragrance, Water.

Other Information

Protect the product from excessive heat and direct sun.

Questions? Contact (626) 616-5811

PRINCIPAL DISPLAY PANEL

COCO & EVE

SUNNY
HONEY

TAN BOOSTING ANTI-AGING

BODY OIL SPF 30

UVA + UVB

Broad Spectrum SPF 30

Net 150 mL / e 5.07 fl. oz. US

COCO & EVE

SUNNY
HONEY

TAN BOOSTING ANTI-AGING

BODY OIL SPF 30

UVA + UVB

Broad Spectrum SPF 30

Tanning Peptides

Net 150 mL / e 5.07 fl. oz. US